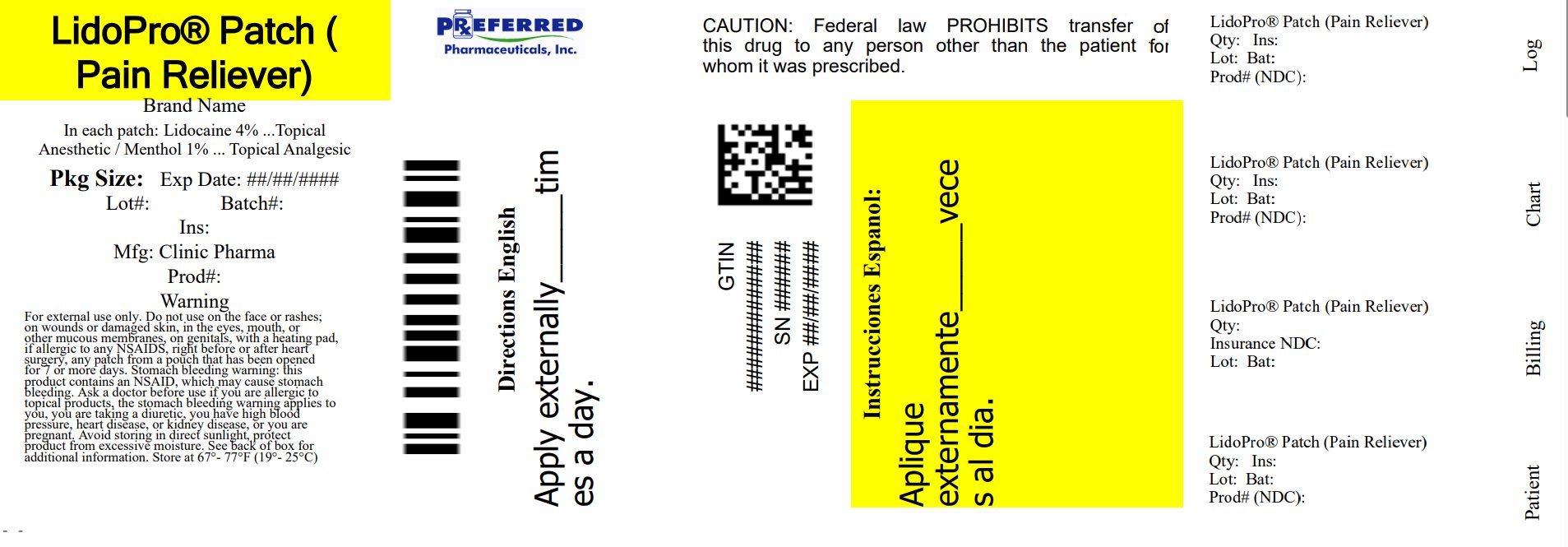 DRUG LABEL: LidoPro Patch (Lidocaine 4%, Menthol 1%)
NDC: 68788-8879 | Form: PATCH
Manufacturer: Preferred Pharmaceuticals Inc.
Category: otc | Type: HUMAN OTC DRUG LABEL
Date: 20250520

ACTIVE INGREDIENTS: MENTHOL, UNSPECIFIED FORM 84 mg/8400 mg; LIDOCAINE 336 mg/8400 mg
INACTIVE INGREDIENTS: GLYCERIN; POLYSORBATE 80; METHYLPARABEN; SODIUM POLYACRYLATE (8000 MW); TARTARIC ACID; WATER; DIHYDROXYALUMINUM AMINOACETATE; POLYACRYLIC ACID (8000 MW); PROPYLPARABEN; SODIUM POLYACRYLATE (2500000 MW); KAOLIN; EDETATE SODIUM; TITANIUM DIOXIDE; PROPANEDIOL; CARBOXYMETHYLCELLULOSE SODIUM, UNSPECIFIED

83881-402 LidoPro Patch (Lidocaine 4%, Menthol 1%)

Active ingredient

Lidocaine 4%

Menthol 1%

Purpose

External Anesthetic

External Analgesic

Uses

For the temporary relief of pain.

Warnings

For external use only.

Do not use

- on the face or rashes, on wounds or damaged skin
- in the eyes, mouth, or other mucous membranes
- on genitals
- with a heating pad
- right before or after heart surgery
- any patch from a pouch that has been opened for 7 or more days
- in large quantities, particularly over raw surfaces or blistered areas
- if tamper-evident seal is torn, broken, or missing
- more than 2 patches per day unless directed by a doctor
- children under 18 years of age

Ask a doctor before use if you have

- allergies to topical products
- high blood pressure, heart disease, or kidney disease

When using this product

- Avoid contact with eyes. If eye contact occurs, rinse thoroughly with water.
- The risk of heart attack or stroke may increase if you use more than directed or for longer than directed.

Stop use and ask doctor if

condition worsens, or if symptoms persist for more than 7 days or clear up and occur again within a few days.

If pregnant of breast-feeding, ask a health professional before use

Do not use during last 3 months of pregnancy because it may cause problems in the unborn child or complications during delivery.

Keep out of reach of children.

If put in mouth, seek medical help or contact a Poison Control Center right away. Dispose if the used patches by folding sticky ends together.

Directions

Adults 18 years and older:

- clean and dry affected area
- open pouch and remove one patch
- remove protective film from patch
- apply one patch to the affected area of pain and leave in place for 8 to 12 hours

Other information

- Some individuals may not experience pain relief until several minutes or hours after applying the patch
- avoid storing product in direct sunlight
- protect product from excessive moisture
- store at 67-77ºF (19-25ºC)

Inactive ingredients

Carboxymethylcellose sodium, Dihydroxyaluminum aminoacetate, Edetate sodium, Glycerin, Kaolin, Methyl parahydroxybenzoate, Partially neutralized Sodium polyacrylate, Polyacrylic acid, Polysorbate 80, Propyl parahydroxybenzoate, Propylene glycol, Sodium Polyacrylate, Tartaric acid, Titanium dioxide, water

Questions?

Call toll-free (800) 224-2048